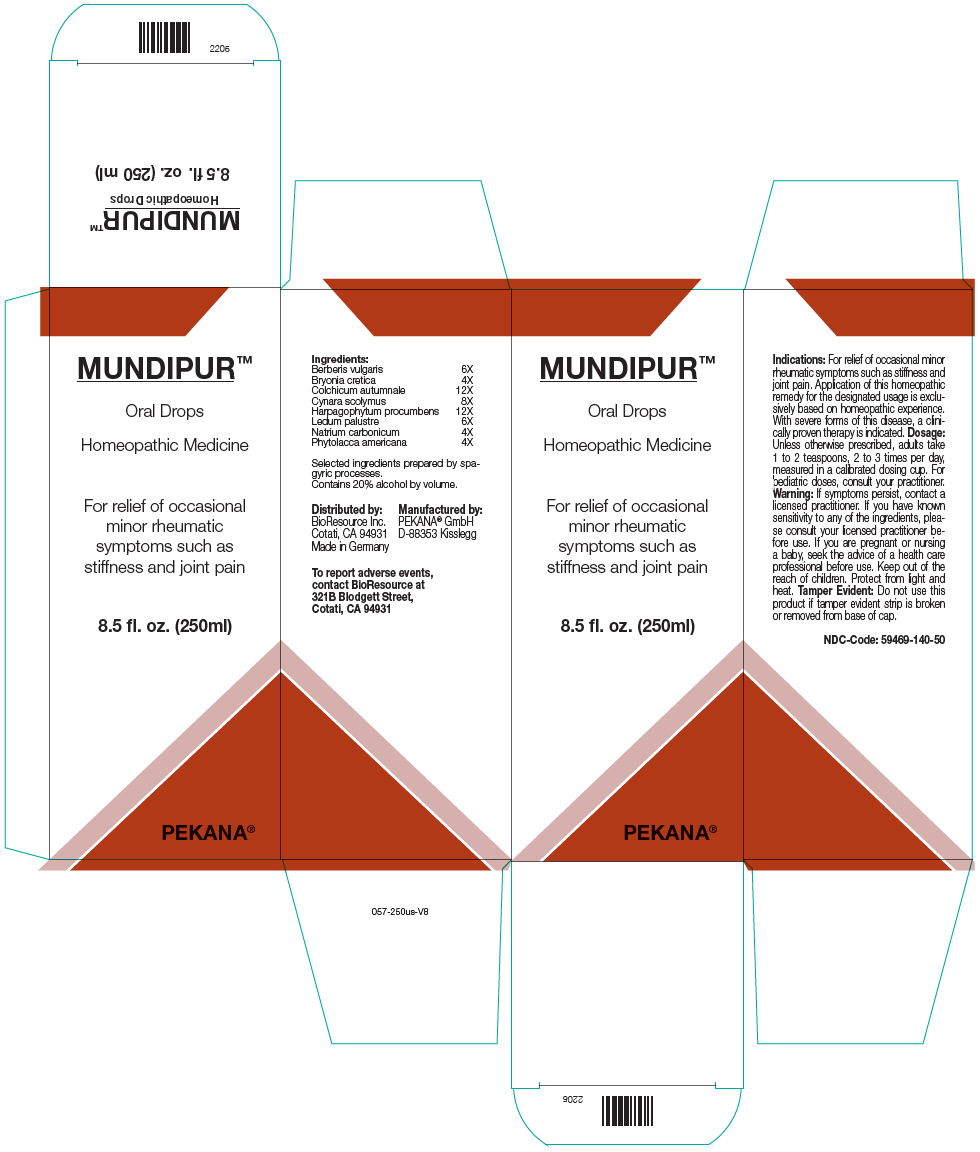 DRUG LABEL: MUNDIPUR
NDC: 59469-140 | Form: SOLUTION/ DROPS
Manufacturer: PEKANA Naturheilmittel GmbH
Category: homeopathic | Type: HUMAN OTC DRUG LABEL
Date: 20221216

ACTIVE INGREDIENTS: Bryonia Dioica Root 4 [hp_X]/250 mL; Colchicum autumnale Bulb 12 [hp_X]/250 mL; Sodium Carbonate 4 [hp_X]/250 mL; Phytolacca americana Root 4 [hp_X]/250 mL; Berberis Vulgaris Root Bark 6 [hp_X]/250 mL; Cynara scolymus Whole 8 [hp_X]/250 mL; Harpagophytum procumbens Root 12 [hp_X]/250 mL; Rhododendron Tomentosum Leafy Twig 6 [hp_X]/250 mL
INACTIVE INGREDIENTS: Water; Alcohol

MUNDIPUR™

ACTIVE INGREDIENT

Ingredients:
Berberis vulgaris | 6X
Bryonia cretica | 4X
Colchicum autumnale | 12X
Cynara scolymus | 8X
Harpagophytum procumbens | 12X
Ledum palustre | 6X
Natrium carbonicum | 4X
Phytolacca americana | 4X

Selected ingredients prepared by spagyric processes.

INACTIVE INGREDIENT

Contains 20% alcohol by volume.

Indications

PURPOSE

For relief of occasional minor rheumatic symptoms such as stiffness and joint pain. Application of this homeopathic remedy for the designated usage is exclusively based on homeopathic experience. With severe forms of this disease, a clinically proven therapy is indicated.

Dosage

Unless otherwise prescribed, adults take 15-20 drops, 3 times per day. For pediatric dosages, consult your practitioner.

Warning

ASK DOCTOR

If symptoms persist, contact a licensed practitioner. If you have known sensitivity to any of the ingredients, please consult your licensed practitioner before use. If you are pregnant or nursing a baby, seek the advice of a health care professional before use.

Keep out of the reach of children.

STORAGE AND HANDLING

Protect from light and heat.

Tamper Evident

Do not use this product if tamper evident strip is broken or removed from base of cap.

QUESTIONS

To report adverse events, contact BioResource at 321B Blodgett Street, Cotati, CA 94931

Distributed by:
BioResource Inc.
Cotati, CA 94931

Manufactured by:
PEKANA® GmbH
D-88353 Kisslegg

PRINCIPAL DISPLAY PANEL - 250 ml Bottle Box

MUNDIPUR™

Oral Drops

Homeopathic Medicine

For relief of occasional
minor rheumatic
symptoms such as
stiffness and joint pain

8.5 fl. oz. (250ml)

PEKANA®